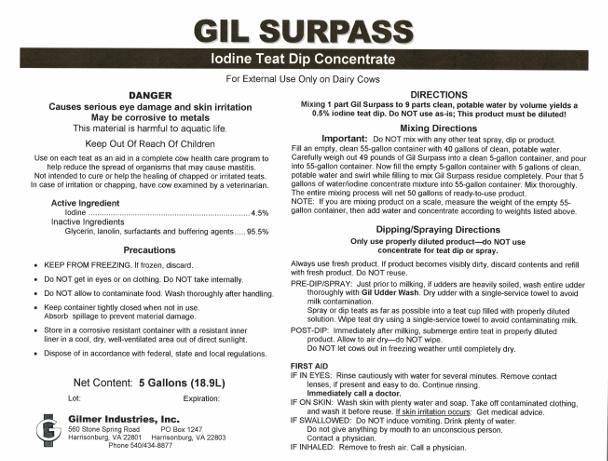 DRUG LABEL: Gil Surpass
NDC: 54420-013 | Form: LIQUID
Manufacturer: Gilmer Industries, Inc.
Category: animal | Type: OTC ANIMAL DRUG LABEL
Date: 20170123

ACTIVE INGREDIENTS: IODINE 45000 mg/1 L

Gil Surpass

PURPOSE

Use on each teat as an aid in a complete cow health care program to help reduce the spread of organisms that may cause mastitis.

Not intended to cure or help the healing of chapped or irritated teats.

In case of irritation or chapping, have cow examined by a veterinarian.

Active Ingredient

Iodine ...................................................................... 4.5%

Inactive Ingredients

Glycerin, lanolin, surfactants and buffering agents.... 95.5%

USER SAFETY WARNINGS

DANGER

- Causes serious eye damage and skin irritation
- May be corrosive to metals
- This material is harmful to aquatic life.

Keep Out Of Reach Of Children

PRECAUTIONS

- KEEP FROM FREEZING. If frozen, discard.
- Do NOT get in eyes or on clothing. Do NOT take internally.
- Do NOT allow to contaminate food. Wash thoroughly after handling.
- Keep container tightly closed when not in use. Absorb spillage to prevent material damage.
- Store in a corrosive resistant container with a resistant inner liner in a cool, dry, well-ventilated area out of direct sunlight.
- Dispose of in accordance with federal, state and local regulations.

FIRST AID

IF IN EYES: Rinse cautiously with water for several minutes.
Remove contact lenses, if present and easy to do. Continue rinsing.
Immediately call a doctor.

IF ON SKIN: Wash skin with plenty water and soap.
Take off contaminated clothing, and wash it before reuse.
If skin irritation occurs: Get medical advice.

IF SWALLOWED: Do NOT induce vomiting. Drink plenty of water.
Do not give anything by mouth to an unconscious person.
Contact a physician.

IF INHALED: Remove to fresh air. Call a physician.

DIRECTIONS

Mixing 1 part Gil Surpass to 9 parts clean, potable water by volume yields a 0.5% iodine teat dip.
Do NOT use as-is; This product must be diluted!

Mixing Directions

Important: Do NOT mix with any other teat spray, dip or product.
Fill an empty, clean 55-gallon container with 40 gallons of clean, potable water. Carefully weigh out 49 pounds of Gil Surpass into a clean 5-gallon container, and pour into 55-gallon container. Now fill the empty 5-gallon container with 5 gallons of clean, potable water and swirl while filling to mix Gil Surpass residue completely. Pour that 5 gallons of water/iodine concentrate mixture into 55-gallon container. Mix thoroughly. The entire mixing process will net 50 gallons of ready-to-use product.
NOTE: If you are mixing product on a scale, measure the weight of the empty 55-gallon container, then add water and concentrate according to weights listed above.

Dipping/Spraying Directions

Only use properly diluted product—do NOT use concentrate for teat dip or spray.
Always use fresh product. If product becomes visibly dirty, discard contents and refill with fresh product. Do NOT reuse.

PRE-DIP/SPRAY: Just prior to milking, if udders are heavily soiled, wash entire udder thoroughly with Gil Udder Wash. Dry udder with a single-service towel to avoid milk contamination.
Spray or dip teats as far as possible into a teat cup filled with properly diluted solution. Wipe teat dry using a single-service towel to avoid contaminating milk.

POST-DIP: Immediately after milking, submerge entire teat in properly diluted product. Allow to air dry—do NOT wipe.
Do NOT let cows out in freezing weather until completely dry.